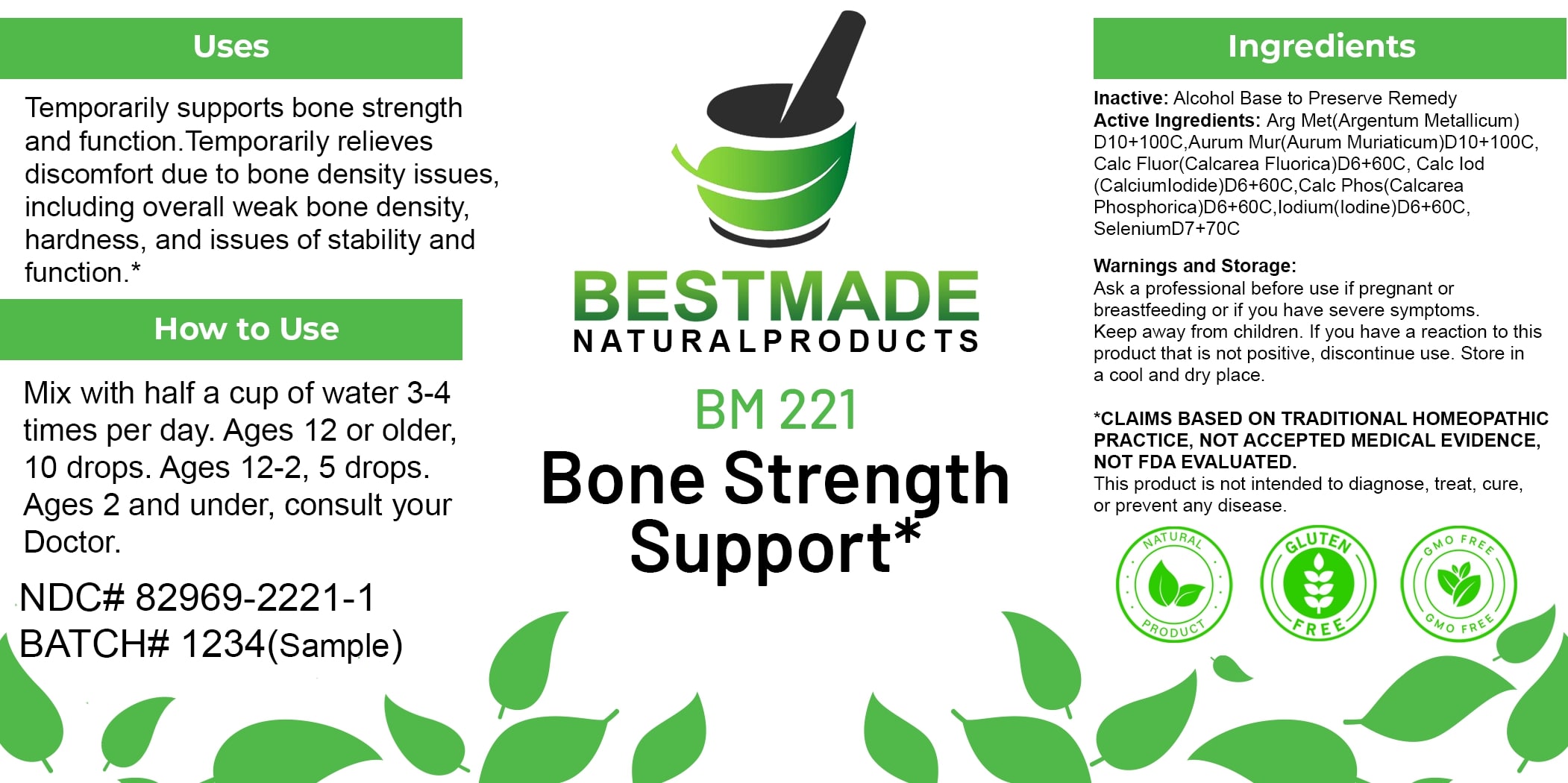 DRUG LABEL: Bestmade Natural Products BM221
NDC: 82969-2221 | Form: LIQUID
Manufacturer: Bestmade Natural Products
Category: homeopathic | Type: HUMAN OTC DRUG LABEL
Date: 20250303

ACTIVE INGREDIENTS: GOLD TRICHLORIDE 30 [hp_C]/30 [hp_C]; CALCIUM IODIDE 30 [hp_C]/30 [hp_C]; TRIBASIC CALCIUM PHOSPHATE 30 [hp_C]/30 [hp_C]; SELENIUM 30 [hp_C]/30 [hp_C]; CALCIUM FLUORIDE 30 [hp_C]/30 [hp_C]; IODINE 30 [hp_C]/30 [hp_C]; SILVER 30 [hp_C]/30 [hp_C]
INACTIVE INGREDIENTS: ALCOHOL 30 [hp_C]/30 [hp_C]

BM221

DOSAGE AND ADMINISTRATION

How to Use

Mix with half a cup of water 3-4 times per day. Ages 12 or older, 10 drops. Ages 12-2, 5 drops. Ages 2 and under, consult your Doctor.

INACTIVE INGREDIENT

Ingredients

Inactive: Alcohol Base to Preserve Remedy

ACTIVE INGREDIENT

Active Ingredients: Arg Met(Argentum Metallicum) D10+100C, Aurum Mur(Aurum Muriaticum)D10+100C, Calc Fluor(Calcarea Fluorica)D6+60C, Calc Iod (Calcium Iodide)D6+60C, Calc Phos(Calcarea Phosphorica)D6+60C, Iodium(Iodine)D6+60C, SeleniumD7+70C

KEEP OUT OF REACH OF CHILDREN

Warnings and Storage:

Ask a professional before use if pregnant or breastfeeding or if you have severe symptoms. Keep away from children. If you have a reaction to this product that is not positive, discontinue use. Store in a cool and dry place.

Warnings and Storage:

Ask a professional before use if pregnant or breastfeeding or if you have severe symptoms. Keep away from children. If you have a reaction to this product that is not positive, discontinue use. Store in a cool and dry place.

*CLAIMS BASED ON TRADITIONAL HOMEOPATHIC PRACTICE, NOT ACCEPTED MEDICAL EVIDENCE. NOT FDA EVALUATED.

This product is not intended to diagnose, treat, cure, or prevent any disease.

Uses

Temporarily supports bone strength and function. Temporarily relieves discomfort due to bone density issues, including overall weak bone density, hardness, and issues of stability and function.*

*CLAIMS BASED ON TRADITIONAL HOMEOPATHIC PRACTICE, NOT ACCEPTED MEDICAL EVIDENCE. NOT FDA EVALUATED.

This product is not intended to diagnose, treat, cure, or prevent any disease.

Uses

Temporarily supports bone strength and function. Temporarily relieves discomfort due to bone density issues, including overall weak bone density, hardness, and issues of stability and function.*

*CLAIMS BASED ON TRADITIONAL HOMEOPATHIC PRACTICE, NOT ACCEPTED MEDICAL EVIDENCE. NOT FDA EVALUATED.

This product is not intended to diagnose, treat, cure, or prevent any disease.

Entire package label